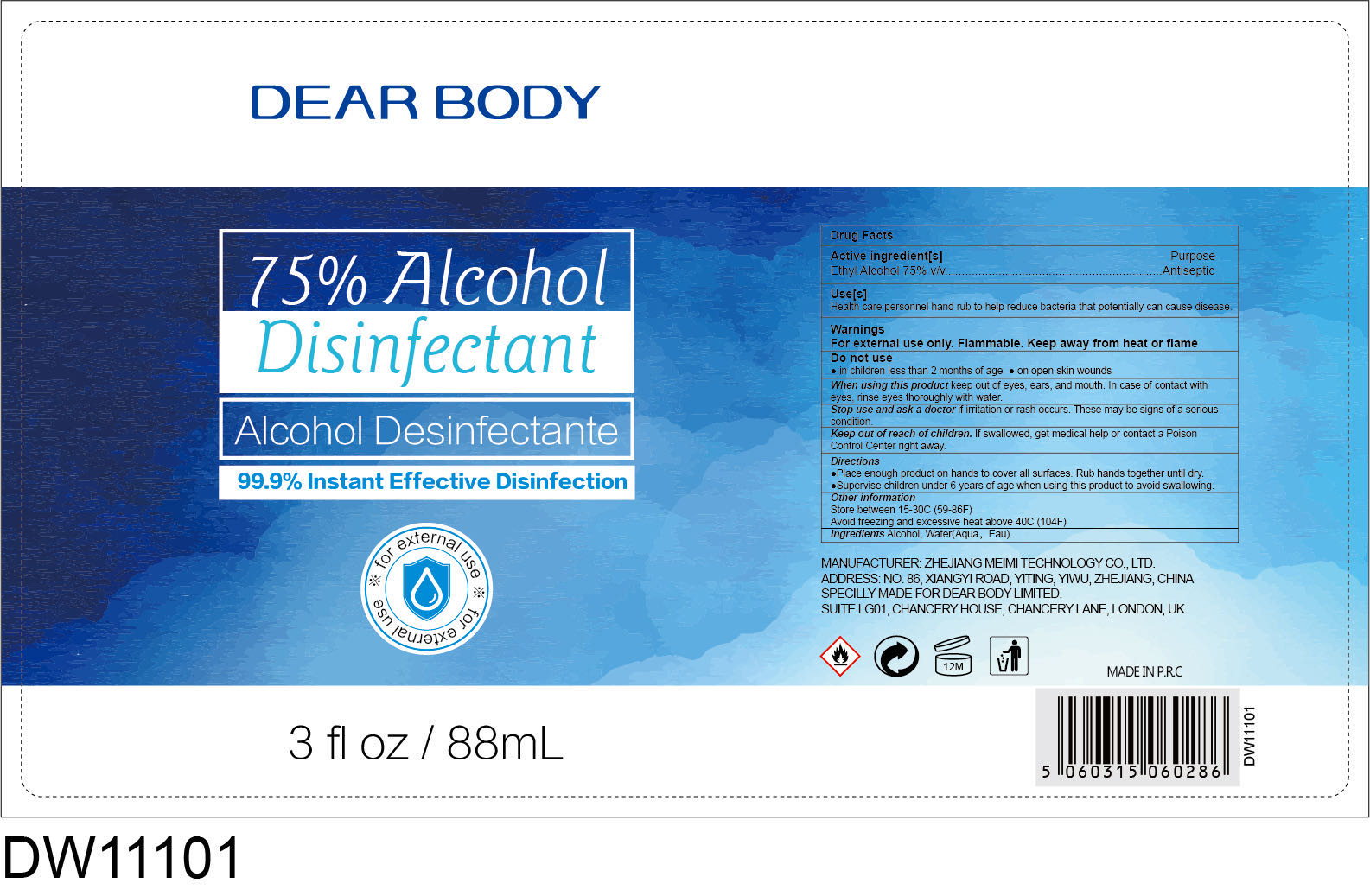 DRUG LABEL: 75% Alcohol Disinfectant
NDC: 41366-015 | Form: LIQUID
Manufacturer: Zhejiang Meimi Technology Co., Ltd.
Category: otc | Type: HUMAN OTC DRUG LABEL
Date: 20251206

ACTIVE INGREDIENTS: ALCOHOL 75 mL/100 mL
INACTIVE INGREDIENTS: WATER

Zhejiang Meimi Technology Co., Ltd.
75% Alcohol Disinfectant
88ml 41366-015-01

Active Ingredient(s)

Ethyl Alcohol 75% v/v

Purpose

Antiseptic

Use

Health care personnel hand rub to help reduce bacteria that potentially can cause disease.

Warnings

- For external use only.
- Flammable. Keep away from heat or flame.

Do not use

- in children less than 2 months of age
- on open skin wounds

When using this product keep out of eyes, ears, and mouth. In case of contact with eyes, rinse eyes thoroughly with water.

Stop use and ask a doctor if irritation or rash occurs.

Keep out of reach of children. If swallowed, get medical help or contact a Poison Control Center right away.

Directions

- Place enough product on hands to cover all surfaces. Rub hands together until dry.
- Supervise children under 6 years of age when using this product to avoid swallowing.

Other information

- Store between 15-30℃(59-86℉)
- Avoid freezing and excessive heat above 40℃(104℉)

Inactive ingredients

Water(Aqua, Eau).

Package Label - Principal Display Panel

88 mL in 1 BOTTLE NDC: 41366-015-01